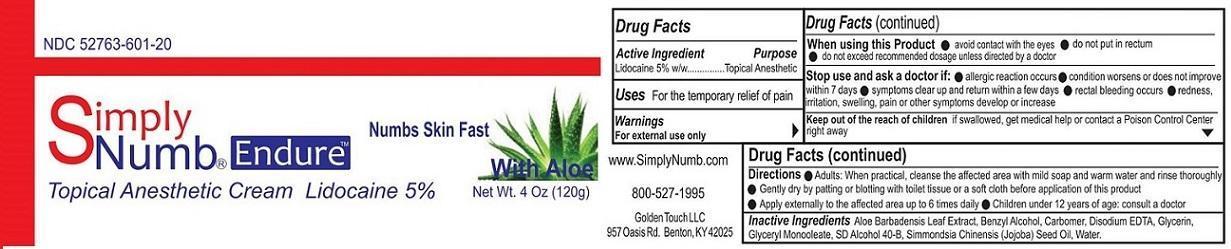 DRUG LABEL: Simply Numb Endure
NDC: 52763-601 | Form: CREAM
Manufacturer: Golden Touch LLC
Category: otc | Type: HUMAN OTC DRUG LABEL
Date: 20151112

ACTIVE INGREDIENTS: LIDOCAINE 5 g/100 g
INACTIVE INGREDIENTS: ALOE VERA LEAF; BENZYL ALCOHOL; CARBOMER HOMOPOLYMER TYPE C (ALLYL PENTAERYTHRITOL CROSSLINKED); EDETATE DISODIUM; GLYCERIN; GLYCERYL OLEATE; ALCOHOL; SIMMONDSIA CHINENSIS SEED; WATER

Simply Numb Endure

Active ingredient

Lidocaine 5% W/W

Purpose

Topical Anesthetic

Keep out of reach of children. If swallowed, get medical help or contact a Poison Control Center right away.

Uses

For the temporary relief of pain

Warnings

For external use only
When using this product

- Avoid contact with the eyes
- Do not put in rectum
- Do not exceed recommended dosage unless directed by a doctor

Stop use and ask a doctor if

- allergic reaction occurs
- condition worsens or does not improve within 7 days
- Symptoms clear up and return within a few days
- rectal bleading occurs
- redness irritation swelling pain or other symptoms develop or increase

Directions

- Adults when practical, cleanse the affected area with mild soap and warm water and rinse thoroughly
- Gently dry by patting or blotting with toilet tissue or a soft cloth before application of this product
- Apply externally to the affected area up to 6 times daily.
- Children under 12 years of age: consult a doctor

Inactive ingredients

Aloe Barbadensis Leaf Extract, Benzyl Alcohol, Carbomer, Disodium EDTA, Glycerin, Glyceryl Monooleate, SD Alcohol 40-B, Simmondsia Chinensis (Jojoba) Seed Oil, Water